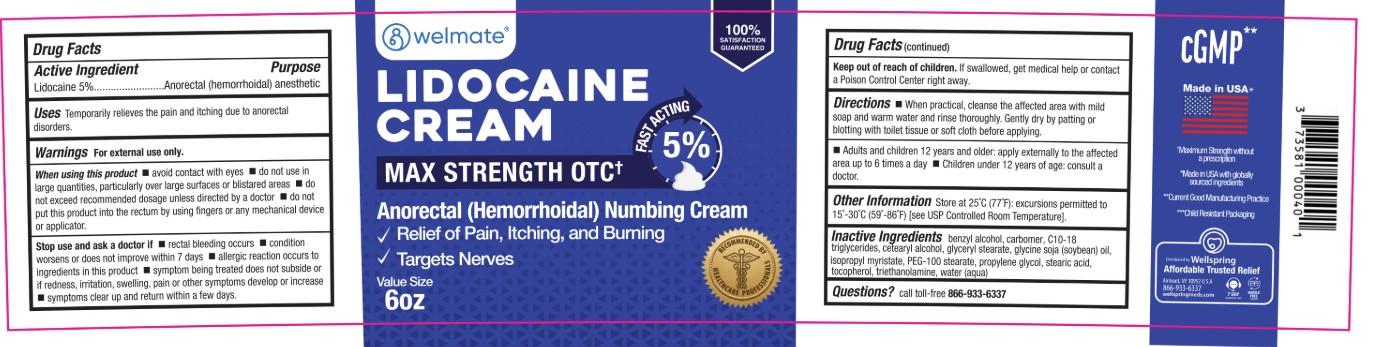 DRUG LABEL: Lidocaine
NDC: 73581-114 | Form: CREAM
Manufacturer: YYBA Corp
Category: otc | Type: HUMAN OTC DRUG LABEL
Date: 20251230

ACTIVE INGREDIENTS: LIDOCAINE 5 g/100 mL
INACTIVE INGREDIENTS: C10-18 TRIGLYCERIDES; PROPYLENE GLYCOL; HYDROGENATED SOYBEAN LECITHIN; TOCOPHEROL; CARBOMER HOMOPOLYMER TYPE C; WATER; POLYSORBATE 80; TROLAMINE; CHOLESTEROL; ISOPROPYL MYRISTATE; BENZYL ALCOHOL

Lidocaine 5% New 6oz WW

Active Ingredient

Lidocaine 5%

Purpose

Anorectal (hemorrhoidal) cream

Usages

Temporarily relieves the pain and itching due to anorectal disorders.

Warnings

For external use only.

When using this product

avoid contact with eyes
do not exceed recommended dosage unlesss directed by a doctor
do not use in large quantaties, particularly over large surfaces or blistered areas
do not put this product into the rectum by using fingers or any medical devices or applicators

Stop and ask a doctor if
rectal bleeding occurs
condition worsens or does not improve within 7 days
allergic reaction occurs to ingredients in the product
symptoms being treated do not subsise or if redness, irritation, swelling, pain or other symptoms develop or increase

symptoms clear up and return within a few days

Flammable
keep away from fire or flame
If pregnant or breast feading, as a health professional before use.

Keep out of reach of children
If swallowed, get medical help or contact a Poison Control Center Right Away

Keep out of reach of children

If swallowed, get medical help or contact a Poison Control Center Right Away

Directions

When practical, cleanse the affected area with mild soap and warm water and rinse thoroughly. Gently dry by patting or

blotting with toilet tissue or soft cloth before applying.

Adults and children 12 years and older: apply externally to the affected area up to 6 times a day
Children under 12 years of age: consult a doctor.

Inactive Ingrediants

benzyl alcohol, carbomer hompolymer type C, Cl 0-18 triglycerides, cholesterol, lecithin, isopropyl myristate,

polysorbate 80, propylene glycol, tocopherol, trolamine, water.